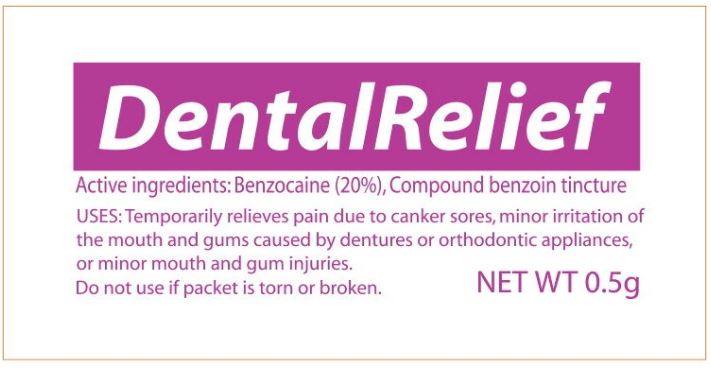 DRUG LABEL: Dental Relief
NDC: 42961-810 | Form: LIQUID
Manufacturer: Cintas Corporation
Category: otc | Type: HUMAN OTC DRUG LABEL
Date: 20250923

ACTIVE INGREDIENTS: benzocaine 200 mg/1 g
INACTIVE INGREDIENTS: polyethylene glycol 400; polyethylene glycol 3350; peppermint oil; saccharin sodium; sorbic acid

Dental Relief

Active Ingredients

Benzocaine 20% (w/w)

Purpose

Oral antiseptic

Uses

For temporary relief of minor pain and sore mouth associated with toothache, minor dental procedures and irritations from dentures or orthodontic appliances.

Warnings

For oral use only

Allergy alert

Do not use this product if you have a history of allergy to local anaesthetics, such as procaine, butacaine, benzocaine, or other “caine” anaesthetics due to the possibility of anaphylactic shock.

When using this product

Do not use for more than 7 days unless directed by a dentist or doctor. If sore mouth symptoms do not improve in 7 days; if irritation, pain or redness persists or worsens; or if swelling, rash, fever or other allergic reaction develops, see your doctor or dentist promptly. Do not exceed recommended dosage.

Keep out of reach of children.

If more than used for pain relief and protection is accidentally swallowed, get medical help or contact a Poison Control Center right away.

Directions

- Adults and children 2 years and older: dry affected area and apply medication undiluted; Use up to 4 times daily, but not more than every two hours, or as directed by a dentist or doctor
- Consult a dentist or doctor for use on children under 2 years of age
- Children under 12 years of should be supervised in the use of this product

Other information

- Do not use if packet is torn, cut or opened
- Store at room temperature, 15° to 30°C (59° to 86°F)
- Avoid contact with eyes

Inactive Ingredients

PEG 400, PEG 3350, peppermint oil, sodium saccharin, sorbic acid

Principal Display Panel – 0.5 gram Packet

Dental Relief

Active ingredients: Benzocaine (20%), Compound benzoin tincture

USES: Temporarily relieves pain due to canker sores, minor irritation of
the mouth and gums caused by dentures or orthodontic appliances,
or minor mouth and gum injuries.

Do not use if packet is torn or broken

NET WT 0.5g